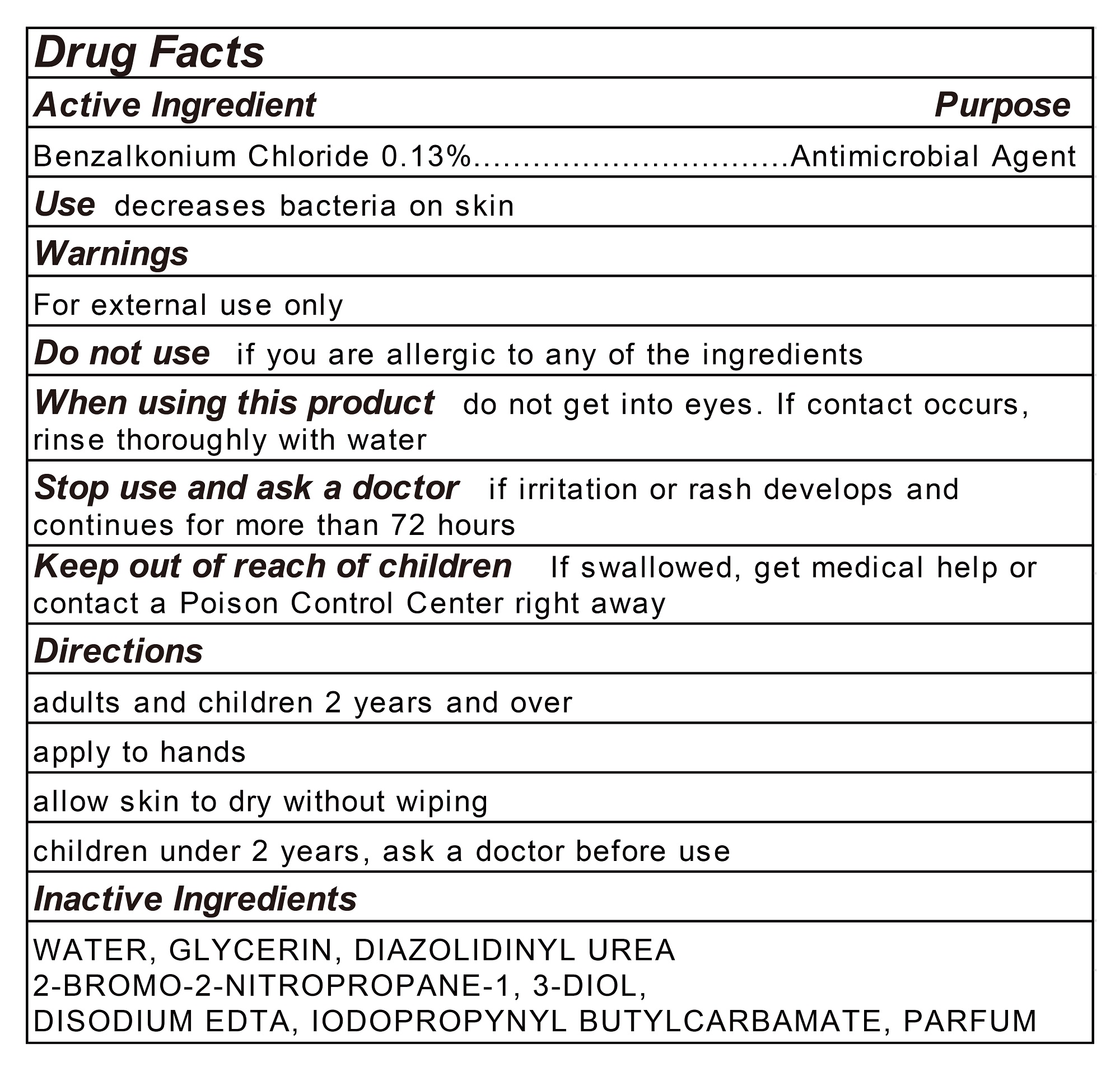 DRUG LABEL: Treasure Wipes
NDC: 78973-001 | Form: CLOTH
Manufacturer: Treasure Health Co.,Ltd.
Category: otc | Type: HUMAN OTC DRUG LABEL
Date: 20200703

ACTIVE INGREDIENTS: BENZALKONIUM CHLORIDE 0.13 g/100 g
INACTIVE INGREDIENTS: IODOPROPYNYL BUTYLCARBAMATE; GLYCERIN; DIAZOLIDINYL UREA; BRONOPOL; EDETATE DISODIUM ANHYDROUS; WATER

78973-001 Treasure Wipes

Active Ingredient

Benzalkonium Chloride 0.13%

Purpose

Antimicrobial Agent

USE

Use decreases bacteria on skin

Warning

For external use only
Do not use if you are allergic to any of the ingredients
When using this product do not get into eyes. If contact occurs ,
rinse thoroughly with water
Stop use and ask a doctor if irritation or rash develops and
continues for more than 72 hours

Keep out of reach of children.
If swallowed, get medical help or contact a Poison Control Center right away.

Directions

adults and children 2 years and over
apply to hands
allow skin to dry without wiping
children under 2 years, ask a doctor before use

Inactive ingredients

WATER, GLYCERIN, DIAZOLIDINYL UREA
2- BROMO-2-NITROPROPANE-1, 3-DIOL，
DISODIUM EDTA, IODOPROPYNYL BUTYL CARBAMATE, PARFUM